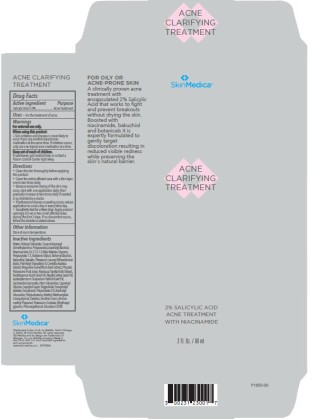 DRUG LABEL: SkinMedica Acne Clarifying Treatment
NDC: 0023-1230 | Form: LOTION
Manufacturer: Allergan, Inc.
Category: otc | Type: HUMAN OTC DRUG LABEL
Date: 20241101

ACTIVE INGREDIENTS: SALICYLIC ACID 20 mg/1 mL
INACTIVE INGREDIENTS: WATER; TRIDECYL SALICYLATE; COCAMIDOPROPYL DIMETHYLAMINE; PROPANEDIOL; ARACHIDYL ALCOHOL; NIACINAMIDE; DI-C12-13 ALKYL MALATE; GLYCERIN; POLYACRYLATE-13; BUTYLENE GLYCOL; BEHENYL ALCOHOL; BAKUCHIOL; BAICALIN; SODIUM LAUROYL OAT AMINO ACIDS; PALMITOYL TRIPEPTIDE-8; CENTELLA ASIATICA TRITERPENOIDS; MAGNOLIA GRANDIFLORA BARK; PHYSALIS PUBESCENS FRUIT JUICE; NARCISSUS TAZETTA BULB; TARAKTOGENOS KURZII SEED OIL; NIGELLA SATIVA SEED OIL; LEPTOSPERMUM SCOPARIUM BRANCH/LEAF OIL; SACCHARIDE ISOMERATE; STEAROYL POLYOXYL-32 GLYCERIDES; CAPRYLOYL GLYCINE; .ALPHA.-TOCOPHEROL ACETATE; TOCOPHEROL; POLYSORBATE 20; ARACHIDYL GLUCOSIDE; POLYISOBUTYLENE (1000 MW); METHYL METHACRYLATE/GLYCOL DIMETHACRYLATE CROSSPOLYMER; DEXTRAN 1; XANTHAN GUM; AMINOMETHYL PROPANOL; POTASSIUM SORBATE; ETHYLHEXYLGLYCERIN; PHENOXYETHANOL; EDETATE DISODIUM

Acne Clarifying Treatment
Drug Facts

Active Ingredient

Salicylic Acid 2%

Purpose

Acne Treatment

Uses

For the treatment of acne.

Warnings

For external use only.

When using this product:

- skin irritation and dryness is more likely to occur if you use another topical acne medication at the same time. If irritation occurs, only use one topical acne medication at a time.

Keep out of reach of children.

If swallowed, get medical help or contact a Poison Control Center right away.

Directions

- Clean the skin thoroughly before applying this product.
- Cover the entire affected area with a thin layer one to three times daily.
- Because excessive drying of the skin may occur, start with one application daily, then gradually increase to two times daily if needed or as directed by a doctor.
- If bothersome dryness or peeling occurs, reduce application to once a day or every other day.
- Sensitivity Test for a New User. Apply product sparingly to one or two small affected areas during the first 3 days. If no discomfort occurs, follow the directions stated above.

Other Information

Store at room temperature

Inactive Ingredients

Water, Tridecyl Salicylate, Cocamidopropyl Dimethylamine, Propanediol, Arachidyl Alcohol, Niacinamide, Di‐C12‐13 Alkyl Malate, Glycerin, Polyacrylate‐13, Butylene Glycol, Behenyl Alcohol, Bakuchiol, Baicalin, Potassium Lauroyl Wheat Amino Acids, Palmitoyl Tripeptide‐8, Centella Asiatica Extract, Magnolia Grandiflora Bark Extract, Physalis Pubescens Fruit Juice, Narcissus Tazetta Bulb Extract, Taraktogenos Kurzii Seed Oil, Nigella Sativa Seed Oil, Leptospermum Scoparium Branch/Leaf Oil, Saccharide Isomerate, Palm Glycerides, Capryloyl Glycine, Caprylic/Capric Triglyceride, Tocopheryl Acetate, Tocopherol, Polysorbate 20, Arachidyl Glucoside, Polyisobutene, Methyl Methacrylate Crosspolymer, Dextran, Xanthan Gum, Aminomethyl Propanol, Potassium Sorbate, Ethylhexylglycerin, Phenoxyethanol, Disodium EDTA

Questions or comments

www.skinmedica.com

Principal Display Panel - Carton

NDC 0023-1230-01

SkinMedica

ACNE CLARIFYING TREATMENT

2% SALICYLIC ACID

ACNE TREATMENT

WITH NIACINAMIDE

2 Fl. Oz. / 60 ml